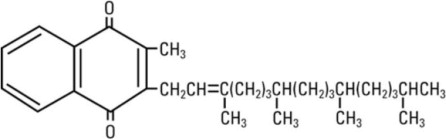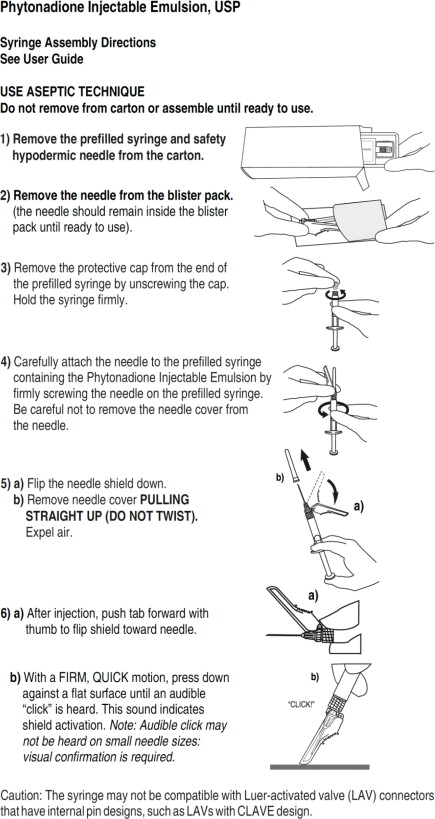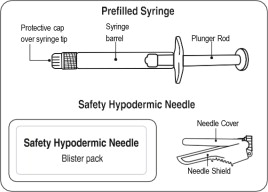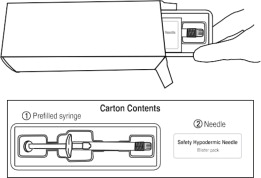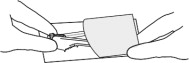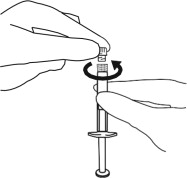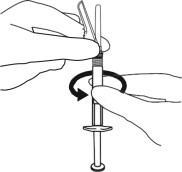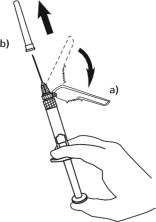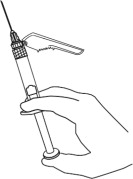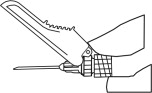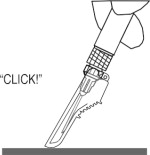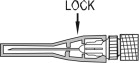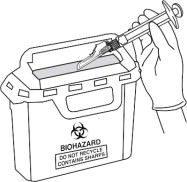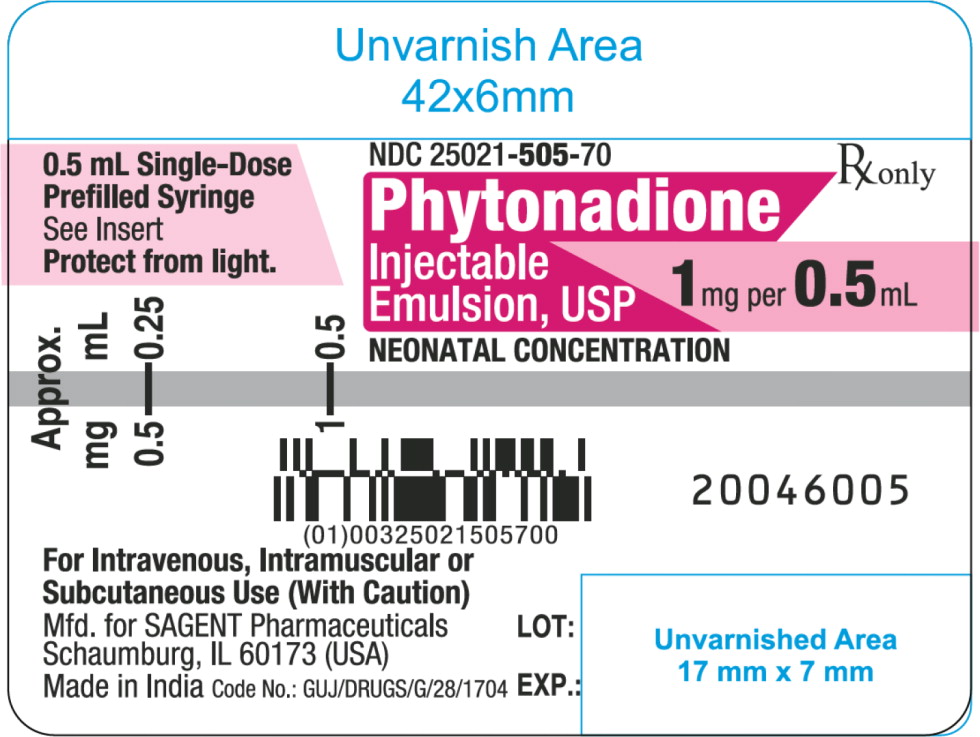 DRUG LABEL: Phytonadione
NDC: 25021-505 | Form: INJECTION, EMULSION
Manufacturer: Sagent Pharmaceuticals
Category: prescription | Type: HUMAN PRESCRIPTION DRUG LABEL
Date: 20260204

ACTIVE INGREDIENTS: Phytonadione 1 mg/0.5 mL
INACTIVE INGREDIENTS: Polysorbate 80; Propylene Glycol; Sodium Acetate Anhydrous; Acetic Acid

HIGHLIGHTS OF PRESCRIBING INFORMATION

These highlights do not include all the information needed to use PHYTONADIONE INJECTABLE EMULSION safely and effectively. See full prescribing information for PHYTONADIONE INJECTABLE EMULSION.
PHYTONADIONE Injection, for intravenous, intramuscular, and subcutaneous use.
Initial U.S. Approval: 1960

WARNING – HYPERSENSITIVITY REACTIONS WITH INTRAVENOUS AND INTRAMUSCULAR USE

See full prescribing information for complete boxed warning.

Fatal hypersensitivity reactions, including anaphylaxis, have occurred during and immediately after INTRAVENOUS and INTRAMUSCULAR injection of Phytonadione Injectable Emulsion. Reactions have occurred despite dilution to avoid rapid infusion and upon first and subsequent doses. Avoid the intravenous and intramuscular routes of administration unless the subcutaneous route is not feasible and the serious risk is justified (5.1)

1 INDICATIONS AND USAGE

Phytonadione Injectable Emulsion is a vitamin K replacement indicated for the treatment of the following coagulation disorders which are due to faulty formation of factors II, VII, IX and X when caused by vitamin K deficiency or interference with vitamin K activity.

- Anticoagulant-induced hypoprothrombinemia deficiency caused by coumarin or indanedione derivatives; (1.1)
- Hypoprothrombinemia due to antibacterial therapy; (1.1)
- Hypoprothrombinemia secondary to factors limiting absorption or synthesis of vitamin K, e.g., obstructive jaundice, biliary fistula, sprue, ulcerative colitis, celiac disease, intestinal resection, cystic fibrosis of the pancreas, and regional enteritis; (1.1)
- Other drug-induced hypoprothrombinemia where is it definitely shown that the result is due to interference with vitamin K metabolism, e.g., salicylates. (1.1)

Phytonadione Injectable Emulsion is indicated for prophylaxis and treatment of vitamin K-deficiency bleeding in neonates. (1.2)

2 DOSAGE AND ADMINISTRATION

- Administer Phytonadione Injectable Emulsion by the subcutaneous route, whenever possible. (2.1)
- When intravenous administration is unavoidable, inject the drug very slowly, not exceeding 1 mg per minute. (2.1)

3 DOSAGE FORMS AND STRENGTHS

Injection: 1 mg per 0.5 mL single-dose prefilled syringe. (3)

4 CONTRAINDICATIONS

Hypersensitivity to any component of this medication. (4)

5 WARNINGS AND PRECAUTIONS

- Cutaneous Reactions: May occur with parenteral use. Discontinue drug and manage medically. (5.3)

6 ADVERSE REACTIONS

Most common adverse reactions are cyanosis, diaphoresis, dizziness, dysgeusia, dyspnea, flushing, hypotension and tachycardia. (6)

To report SUSPECTED ADVERSE REACTIONS, contact Sagent Pharmaceuticals at 1-866-625-1618 or FDA at 1-800-FDA-1088 or www.fda.gov/medwatch.

7 DRUG INTERACTIONS

Anticoagulants: May induce temporary resistance to prothrombin-depressing anticoagulants. (7)

8 USE IN SPECIFIC POPULATIONS

- Pregnancy: If available, use the preservative-free formulation in pregnant women. (8.1)
- Lactation: If available, use the preservative-free formulation in lactating women. (8.2)
- Pediatric Use: The safety and effectiveness of Phytonadione Injectable Emulsion in pediatric patients from 6 months to 17 years have not been established. (8.4)

FULL PRESCRIBING INFORMATION

WARNING – HYPERSENSITIVITY REACTIONS WITH INTRAVENOUS AND INTRAMUSCULAR USE

Fatal hypersensitivity reactions, including anaphylaxis, have occurred during and immediately after intravenous and intramuscular injection of Phytonadione Injectable Emulsion. Reactions have occurred despite dilution to avoid rapid intravenous infusion and upon first dose. Avoid the intravenous and intramuscular routes of administration unless the subcutaneous route is not feasible and the serious risk is justified [see WARNINGS AND PRECAUTIONS (5.1)].

1 INDICATIONS AND USAGE

1.1 Treatment of Hypoprothrombinemia Due to Vitamin K Deficiency or Interference

Phytonadione Injectable Emulsion is indicated for the treatment of the following coagulation disorders which are due to faulty formation of factors II, VII, IX and X when caused by vitamin K-deficiency or interference with vitamin K activity:

- anticoagulant-induced hypoprothrombinemia caused by coumarin or indanedione derivatives;
- hypoprothrombinemia due to antibacterial therapy;
- hypoprothrombinemia secondary to factors limiting absorption or synthesis of vitamin K, e.g., obstructive jaundice, biliary fistula, sprue, ulcerative colitis, celiac disease, intestinal resection, cystic fibrosis of the pancreas, and regional enteritis;
- other drug-induced hypoprothrombinemia where it is definitely shown that the result is due to interference with vitamin K metabolism, e.g., salicylates.

1.2 Prophylaxis and Treatment of Vitamin K-Deficiency Bleeding in Neonates

Phytonadione Injectable Emulsion is indicated for prophylaxis and treatment of vitamin K deficiency bleeding in neonates.

2 DOSAGE AND ADMINISTRATION

2.1 Dosing Considerations

Whenever possible, administer Phytonadione Injectable Emulsion by the subcutaneous route [see Boxed Warning]. When intravenous administration is unavoidable, inject the drug very slowly, not exceeding 1 mg per minute [see WARNINGS AND PRECAUTIONS (5.1)].

Monitor international normalized ratio (INR) regularly and as clinical conditions indicate. Use the lowest effective dose of Phytonadione Injectable Emulsion.

The coagulant effects of Phytonadione Injectable Emulsion are not immediate; improvement of INR may take 1 to 8 hours. Interim use of whole blood or component therapy may also be necessary if bleeding is severe.

When Phytonadione Injectable Emulsion is used to correct excessive anticoagulant-induced hypoprothrombinemia, anticoagulant therapy still being indicated, the patient is again faced with the clotting hazards existing prior to starting the anticoagulant therapy. Phytonadione Injectable Emulsion is not a clotting agent, but overzealous therapy with Phytonadione Injectable Emulsion may restore conditions which originally permitted thromboembolic phenomena. Dosage should be kept as low as possible, and INR should be checked regularly as clinical conditions indicate.

2.2 Recommended Dosage for Coagulation Disorders from Vitamin K Deficiency or Interference

The recommended dosage of Phytonadione Injectable Emulsion is based on whether the hypoprothrombinemia is anticoagulant-induced (e.g., due to coumarin or indanedione derivatives) or non-anticoagulant-induced (e.g., due to antibiotics; salicylates or other drugs; factors limiting absorption or synthesis) as follows:

- Anticoagulant-Induced Hypoprothrombinemia: Phytonadione Injectable Emulsion 2.5 mg to 10 mg or more subcutaneously, intramuscularly, or intravenously. Up to 25 mg to 50 mg may be administered as a single dose.

Repeated large doses of Phytonadione Injectable Emulsion are not warranted in liver disease if the initial response is unsatisfactory. Failure to respond to Phytonadione Injectable Emulsion may indicate that the condition being treated is inherently unresponsive to Phytonadione Injectable Emulsion.

- Hypoprothrombinemia Due to Other Causes (Non-Anticoagulation-Induced Hypoprothrombinemia): Phytonadione Injectable Emulsion 2.5 mg to 25 mg or more intravenously, intramuscularly, or subcutaneously. Up to 50 mg may be administered as a single dose.

Evaluate INR after 6 to 8 hours, and repeat dose if INR remains prolonged. Modify subsequent dosage (amount and frequency) based on the INR or clinical condition.

2.3 Recommended Dosage for Prophylaxis and Treatment of Vitamin K Deficiency Bleeding in Neonates

Prophylaxis of Vitamin K-Deficiency Bleeding in Neonates

The recommended dosage of Phytonadione Injectable Emulsion is 0.5 mg to 1 mg within one hour of birth for a single dose.

Treatment of Vitamin K Deficiency Bleeding in Neonates

The recommended dosage of Phytonadione Injectable Emulsion is 1 mg given either subcutaneously or intramuscularly.

Consider higher doses if the mother has been receiving oral anticoagulants.

A failure to respond (shortening of the INR in 2 to 4 hours) may indicate another diagnosis or coagulation disorder.

2.4 Directions for Dilution

Caution: The syringe may not be compatible with Luer-activated valve (LAV) connectors that have internal pin designs, such as LAVs with CLAVE design.

Dilute Phytonadione Injectable Emulsion with 0.9% Sodium Chloride Injection, 5% Dextrose Injection, or 5% Dextrose and Sodium Chloride Injection.

When diluted, start administration of Phytonadione Injectable Emulsion immediately after dilution.

Discard unused portions of diluted solution as well as unused contents of the pre-filled syringe.

Protect Phytonadione Injectable Emulsion from light at all times.

Parenteral drug products should be inspected visually for particulate matter and discoloration prior to administration, whenever solution and container permit.

3 DOSAGE FORMS AND STRENGTHS

Injection: 1 mg per 0.5 mL single-dose prefilled syringe.

4 CONTRAINDICATIONS

Hypersensitivity to phytonadione or any other component of this medication [see WARNINGS AND PRECAUTIONS (5.1)].

5 WARNINGS AND PRECAUTIONS

5.1 Hypersensitivity Reactions

Fatal and severe hypersensitivity reactions, including anaphylaxis, have occurred with intravenous or intramuscular administration of Phytonadione Injectable Emulsion. Reactions have occurred despite dilution to avoid rapid intravenous infusion and upon first dose. These reactions have included shock, cardiorespiratory arrest, flushing, diaphoresis, chest pain, tachycardia, cyanosis, weakness, and dyspnea. Administer Phytonadione Injectable Emulsion subcutaneously whenever feasible. Avoid the intravenous and intramuscular routes of administration unless the subcutaneous route is not feasible and the serious risk is justified [see DOSAGE AND ADMINISTRATION (2.1)].

5.3 Cutaneous Reactions

Parenteral administration of vitamin K replacements (including Phytonadione Injectable Emulsion) may cause cutaneous reactions. Reactions have included eczematous reactions, scleroderma-like patches, urticaria, and delayed-type hypersensitivity reactions. Time of onset ranged from 1 day to a year after parenteral administration. Discontinue Phytonadione Injectable Emulsion for skin reactions and institute medical management.

6 ADVERSE REACTIONS

The following serious adverse reactions are described elsewhere in the labeling:

- Hypersensitivity Reactions [see WARNINGS AND PRECAUTIONS (5.1)]
- Cutaneous Reactions [see WARNINGS AND PRECAUTIONS (5.3)]

6.1 Clinical Trials and Post-Marketing Experience

Because clinical trials are conducted under widely varying conditions, adverse reaction rates observed in the clinical trials of a drug cannot be directly compared to rates in the clinical trials of another drug and may not reflect the rates observed in practice.

The following adverse reactions have been identified during post-approval use of Phytonadione Injectable Emulsion. Because these reactions were reported voluntarily from a population of uncertain size, it is not always possible to reliably estimate their frequency or establish a causal relationship to drug exposure.

Cardiac Disorders: Tachycardia, hypotension.

General disorders and administration site conditions: Generalized flushing; pain, swelling, and tenderness at injection site.

Hepatobiliary Disorders: Hyperbilirubinemia

Immune System Disorders: Fatal hypersensitivity reactions, anaphylactic reactions.

Neurologic: Dysgeusia, dizziness.

Pulmonary: Dyspnea.

Skin and Subcutaneous Tissue Disorders: Erythema, pruritic plaques, scleroderma-like lesions, erythema perstans.

Vascular: Cyanosis.

7 DRUG INTERACTIONS

Anticoagulants

Phytonadione Injectable Emulsion may induce temporary resistance to prothrombin-depressing anticoagulants, especially when larger doses of Phytonadione Injectable Emulsion are used. Should this occur, higher doses of anticoagulant therapy may be needed when resuming anticoagulant therapy, or a change in therapy to a different class of anticoagulant may be necessary (i.e., heparin sodium).

Phytonadione Injectable Emulsion does not affect the anticoagulant action of heparin.

8 USE IN SPECIFIC POPULATIONS

8.1 Pregnancy

Risk Summary

If Phytonadione is needed during pregnancy, consider using a preservative-free formulation.

Published studies with the use of phytonadione during pregnancy have not reported a clear association with phytonadione and adverse developmental outcomes (see Data). There are maternal and fetal risks associated with vitamin K deficiency during pregnancy (see Clinical Considerations). Animal reproduction studies have not been conducted with phytonadione.

The estimated background risk for the indicated population is unknown. All pregnancies have a background risk of birth defect, loss, or other adverse outcomes. In the U.S. general population, the estimated background risk of major birth defects and miscarriage in clinically recognized pregnancies is 2 to 4% and 15 to 20%, respectively.

Clinical Considerations

Disease-associated maternal and/or embryo/fetal risk

Pregnant women with vitamin K deficiency hypoprothrombinemia may be at an increased risk for bleeding diatheses during pregnancy and hemorrhagic events at delivery. Subclinical maternal vitamin K deficiency during pregnancy has been implicated in rare cases of fetal intracranial hemorrhage.

Data

Human Data

Phytonadione has been measured in cord blood of infants whose mothers were treated with phytonadione during pregnancy in concentrations lower than seen in maternal plasma. Administration of vitamin K1 to pregnant women shortly before delivery increased both maternal and cord blood concentrations. Published data do not report a clear association with phytonadione and adverse maternal or fetal outcomes when used during pregnancy. However, these studies cannot definitively establish the absence of any risk because of methodologic limitations including small sample size and lack of blinding.

Animal Data

In pregnant rats receiving vitamin K1 orally, fetal plasma and liver concentrations increased following administration, supporting placental transfer.

8.2 Lactation

Risk Summary

If available, preservative-free Phytonadione is recommended when Phytonadione is needed during lactation [see USE IN SPECIFIC POPULATIONS (8.4)].

Phytonadione is present in breastmilk. There are no data on the effects of Phytonadione Injectable Emulsion on the breastfed child or on milk production. The developmental and health benefits of breastfeeding should be considered along with the clinical need for Phytonadione Injectable Emulsion and any potential adverse effects on the breastfed child from Phytonadione Injectable Emulsion or from the underlying maternal condition.

8.4 Pediatric Use

The safety and effectiveness of Phytonadione Injectable Emulsion for prophylaxis and treatment of vitamin K deficiency have been established in neonates. Use of phytonadione injection for prophylaxis and treatment of vitamin K deficiency is based on published clinical studies.

10 OVERDOSAGE

Hemolysis, jaundice, and hyperbilirubinemia in newborns, particularly in premature infants, may result from Phytonadione Injectable Emulsion overdose.

11 DESCRIPTION

Phytonadione is a vitamin K replacement, which is a clear, yellow to amber, viscous, odorless or nearly odorless liquid. It is insoluble in water, soluble in chloroform and slightly soluble in ethanol. It has a molecular weight of 450.70.

Phytonadione is 2-methyl-3-phytyl-1, 4-naphthoquinone. Its empirical formula is C31H46O2 and its molecular structure is:

Phytonadione Injectable Emulsion, USP injection is a yellow, sterile, aqueous colloidal solution of vitamin K1, with a pH of 4 to 6.5, available for injection by the intravenous, intramuscular, and subcutaneous routes. Phytonadione Injectable Emulsion, USP is available in 1 mg (1 mg per 0.5 mL) single-dose prefilled syringes. Each 0.5 mL of Phytonadione Injectable Emulsion, USP contains the following inactive ingredients: 10 mg polysorbate 80, 10.4 mg propylene glycol, 0.17 mg sodium acetate anhydrous, and 0.00002 mL glacial acetic acid. Additional glacial acetic acid or sodium acetate anhydrous may have been added to adjust pH to meet USP limits of 4 to 6.5.

12 CLINICAL PHARMACOLOGY

12.1 Mechanism of Action

Phytonadione Injectable Emulsion aqueous colloidal solution of vitamin K for parenteral injection, possesses the same type and degree of activity as does naturally-occurring vitamin K, which is necessary for the production via the liver of active prothrombin (factor II), proconvertin (factor VII), plasma thromboplastin component (factor IX), and Stuart factor (factor X). Vitamin K is an essential cofactor for a microsomal enzyme that catalyzes the post-translational carboxylation of multiple, specific, peptide-bound glutamic acid residues in inactive hepatic precursors of factors II, VII, IX, and X. The resulting gamma-carboxy-glutamic acid residues convert the precursors into active coagulation factors that are subsequently secreted by liver cells into the blood.

In normal animals and humans, phytonadione is virtually devoid of activity. However, in animals and humans deficient in vitamin K, the pharmacological action of vitamin K is related to its normal physiological function, that is, to promote the hepatic biosynthesis of vitamin K dependent clotting factors.

12.2 Pharmacodynamics

The action of the aqueous dispersion, when administered intravenously, is generally detectable within an hour or two and hemorrhage is usually controlled within 3 to 6 hours. A normal INR may often be obtained in 12 to 14 hours.

12.3 Pharmacokinetics

Absorption:

Phytonadione is readily absorbed following intramuscular administration.

Distribution:

After absorption, phytonadione is initially concentrated in the liver, but the concentration declines rapidly. Very little vitamin K accumulates in tissues.

Elimination:

Little is known about the metabolic fate of vitamin K. Almost no free unmetabolized vitamin K appears in bile or urine.

13 NONCLINICAL TOXICOLOGY SECTION

13.1 Carcinogenesis, Mutagenesis, Impairment of Fertility

Studies of carcinogenicity, genotoxicity or impairment of fertility have not been conducted with phytonadione.

16 HOW SUPPLIED/STORAGE AND HANDLING

Phytonadione Injectable Emulsion, USP is a yellow, sterile, aqueous colloidal solution and is supplied as follows:

NDC | Phytonadione Injectable Emulsion, USP | Package Factor
25021-505-70 | 1 mg per 0.5 mL Single-Dose Prefilled Syringe | 10 syringes per carton
25021-505-76 | 1 mg per 0.5 mL Single-Dose Prefilled Syringe | 25 syringes per carton

Phytonadione Injectable Emulsion, USP 1 mg in 0.5 mL available in cartons of 10 or 25 mono-cartons; each mono-carton contains one single-dose, prefilled syringe and 27 G. x ½” needle.

Storage Conditions

Store at 20° to 25°C (68° to 77°F); excursions permitted between 15° and 30°C (59° and 86°F). [See USP Controlled Room Temperature.]

Protect from light. Store container in closed original carton until contents have been used.

Discard unused portion.

Sterile, Nonpyrogenic, Preservative-free.
The container closure is not made with natural rubber latex.

17 PATIENT COUNSELING INFORMATION

Advise the patient to read the FDA-approved patient labeling (Patient Information).

Inform the patient of the following important risks of Phytonadione Injectable Emulsion:

Serious Hypersensitivity Reactions

Advise the patient and caregivers to immediately report signs of hypersensitivity after receiving Phytonadione Injectable Emulsion [see WARNINGS AND PRECAUTIONS (5.1)].

Cutaneous Reactions

Advise the patient and caregivers to report the occurrence of new rashes after receiving Phytonadione Injectable Emulsion. These reactions may be delayed for up to a year after treatment [see WARNINGS AND PRECAUTIONS (5.3)].

Rx Only

sagent®
Mfd. for SAGENT Pharmaceuticals
Schaumburg, IL 60173 (USA)
Made in India
©2025 Sagent Pharmaceuticals

October 2025

INSTRUCTIONS FOR USE

Phytonadione Injectable Emulsion, USP USER GUIDE NOTE: USE ASEPTIC TECHNIQUE Do not assemble until ready to use. |  | 4 Remove the protective cap from the end of the prefilled syringe by unscrewing the cap. Hold the syringe firmly.
1 Preparing your dose of Phytonadione Injectable Emulsion; - You will need the following supplies: - Your Phytonadione Injectable Emulsion carton that includes 1 single-use Phytonadione Injectable Emulsion prefilled syringe and 1 safety hypodermic needle. |  | 5 Carefully attach the needle to the prefilled syringe containing the Phytonadione Injectable Emulsion by firmly screwing the needle on the prefilled syringe. Be careful not to remove the needle cover from the needle.
2 Remove the prefilled syringe and safety hypodermic needle from the carton. |  | 6 (a) Flip the needle shield down. (b) Remove needle cover PULLING STRAIGHT UP (DO NOT TWIST). Expel air.
3 Remove the needle from the blister pack (the needle should remain inside the blister pack until ready to use). |  | 11 Following activation of the needle shield, immediately discard the unit into an approved sharps container.
7 Administer injection following the established aseptic technique. |  | Caution: The syringe may not be compatible with Luer-activated valve (LAV) connectors that have internal pin designs, such as LAVs with CLAVE design. For additional questions, contact Customer Service at 1-866-625-1618.
8 After injection, position shield in preparation for device activation: Using a one-handed technique, push the tab forward with your finger or thumb so that the shield is less than 90 degrees from the needle. NOTE: Keep your finger or thumb behind the tab at all times. |  | sagent® Mfd. for SAGENT Pharmaceuticals Schaumburg, IL 60173 (USA) Made in India ©2025 Sagent Pharmaceuticals October 2025
9 Activate shield: Position the shield approximately 45 degrees to flat surface. Press down with a GENTLE, QUICK, MOTION until a distinct AUDIBLE CLICK is heard. Note: Audible click may not be heard on small needle sizes: visual confirmation is required.
10 VISUALLY CONFIRM that needle is fully engaged under lock.

PACKAGE LABEL – PRINCIPAL DISPLAY PANEL – Syringe Label

NDC 25021-505-70

Rx only

Phytonadione Injectable Emulsion, USP

1 mg per 0.5 mL

Neonatal Concentration

0.5 mL Single-Dose Prefilled Syringe

See Insert

Protect from light.

For Intravenous, Intramuscular or Subcutaneous Use (With Caution)